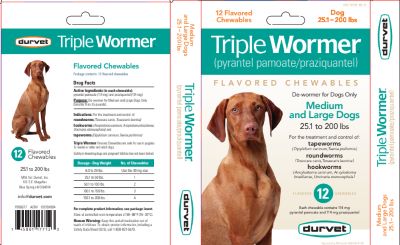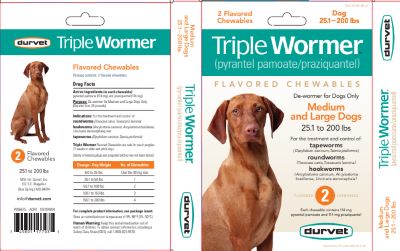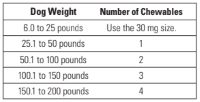 DRUG LABEL: Triple Wormer
NDC: 30798-186 | Form: TABLET, CHEWABLE
Manufacturer: Durvet, Inc.
Category: animal | Type: OTC ANIMAL DRUG LABEL
Date: 20260121

ACTIVE INGREDIENTS: pyrantel pamoate 114 mg/1 1; praziquantel 114 mg/1 1

Triple Wormer® (pyrantel pamoate/praziquantel) Flavored Chewables

Package contents:

Blisters of 2 or 12 flavored chewables

Drug Facts

Active Ingredients
(in each chewable):

pyrantel pamoate (114 mg)

and praziquantel (114 mg)

Purpose: De-wormer for Medium and Large Dogs Only (Greater than 25 pounds).

Uses:

For the treatment and control of:

• Roundworms (Toxocara canis, Toxascaris leonina)

• Hookworms (Ancylostoma caninum, Ancylostoma braziliense, and Uncinaria stenocephala)

• Tapeworms (Dipylidium caninum, Taenia pisiformis)

Human Warning:

Keep this and all medication out of the reach of children. To obtain product information, including a Safety Data Sheet (SDS), call 1-800-821-5570.

When Using This Product:
• Consult your veterinarian for assistance in the diagnosis, treatment, and control of parasitism.

• Do not de-worm a dog or puppy that is sick. Consult a veterinarian for diagnosis of the illness.

• Triple Wormer
Flavored Chewables are safe for use in puppies 12 weeks or older and adult dogs. Safety in breeding dogs and pregnant bitches has not been tested.

You May Notice:

Vomiting, loose stools (with or without blood) and decreased activity following treatment. If you notice these signs, contact a veterinarian.

Directions:

Each flavored chewable contains 114 mg of pyrantel pamoate and 114 mgof praziquantel. The dose for each drug is 2.27 mg per pound of body weight (5 mg/kg). Please refer to the following dosing table for help finding the right dose for your dog.

Triple Wormer Flavored Chewables Dosing Table

• You should weigh your dog to make sure you are giving the right dose.

• Triple Wormer Flavored Chewables are palatable if offered by hand. If your dog does not voluntarily eat the chewable, you can hide the chewable in a small amount of food or place it in the back of the dog's mouth for forced swallowing.
• Make sure that the dog eats the complete dose.
• Watch your dog for a few minutes after dosing to make sure the chewable is not rejected.

Other Information:

Recommended Deworming Schedule: Consult your veterinarian for assistance in the diagnosis, treatment, and control of parasitism. De-worming schedules may vary depending on the climate where you live and the activity of your dog.

Re-treatment: Re-treatment of your dog may be necessary as determined by laboratory fecal examination and/or if your dog is living where re-infections are likely to occur. Consult your veterinarian for assistance in the diagnosis and prevention of re-infection. In case of re-infection with tapeworms (Dipylidium caninum), consult your veterinarian for advice on how to remove fleas from thedog and the environment.

Manufactured for:

Durvet, Inc.
100 S.E. Magellan Drive
Blue Springs, MO 64014

Storage:

Store at controlled room temperature of 59-86°F (15-30°C).

Questions? Comments?

To report a suspected adverse reaction, call 1-800-821-5570.

P002622-3 AMRV

Approved by FDA under NADA #141-261